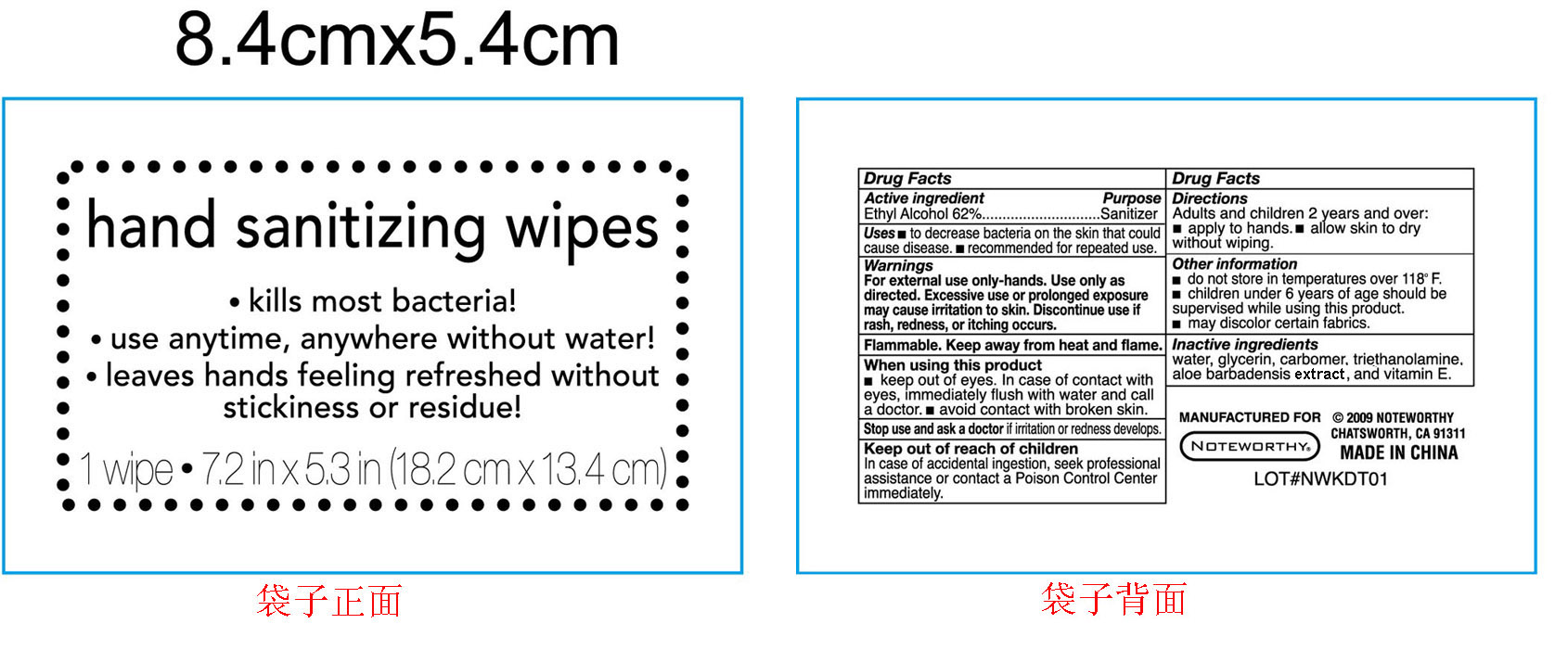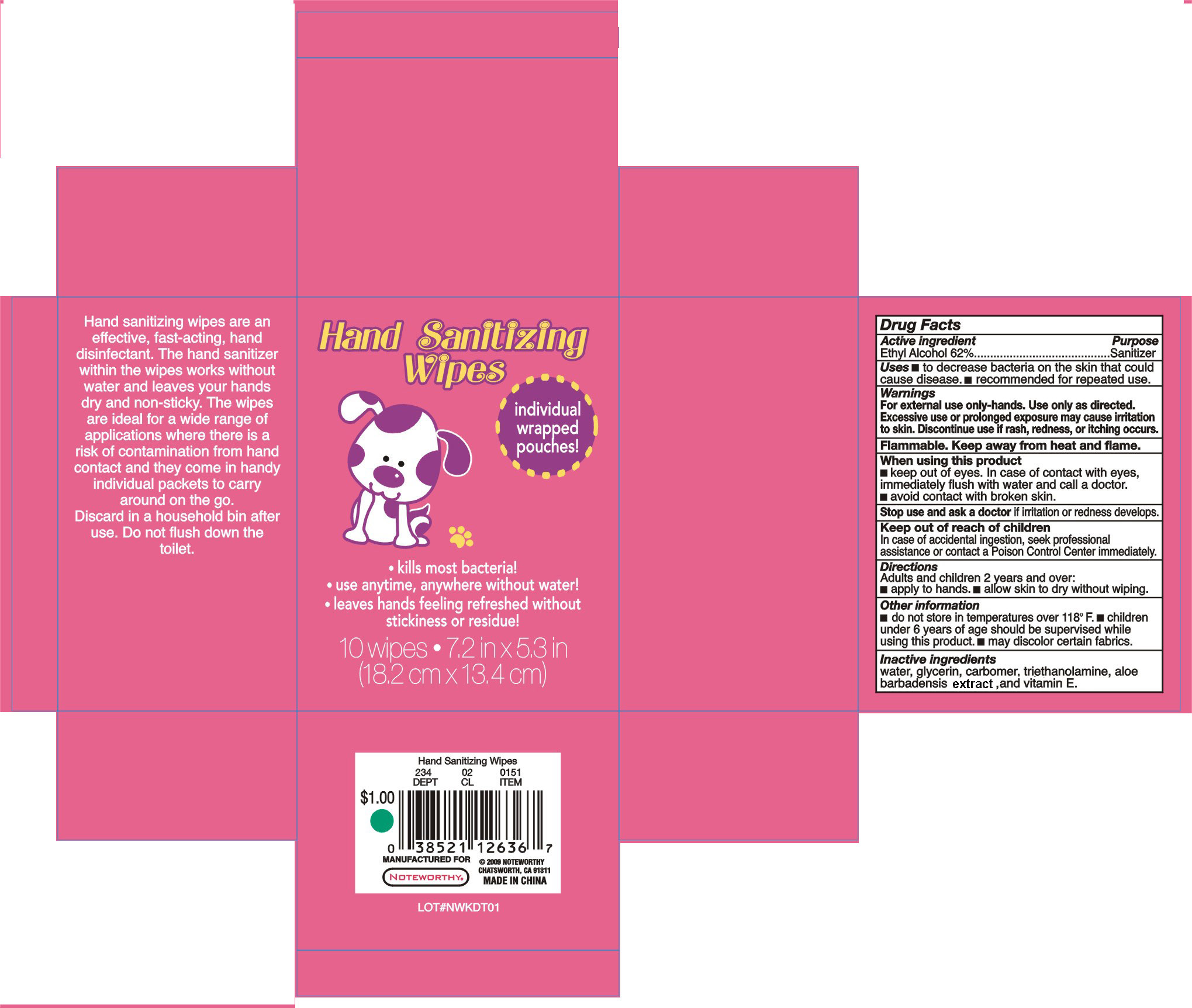 DRUG LABEL: Hand Sanitizing Wipes
NDC: 25225-016 | Form: CLOTH
Manufacturer: Unique Holding Group Inc
Category: otc | Type: HUMAN OTC DRUG LABEL
Date: 20100503

ACTIVE INGREDIENTS: ALCOHOL 62 1/100 1
INACTIVE INGREDIENTS: Water 36.955 1/100 1; Glycerin 1 1/100 1; ALOE VERA LEAF 0.005 1/100 1; CARBOMER HOMOPOLYMER TYPE C 0.02 1/100 1; ALPHA-TOCOPHEROL 0.005 1/100 1; TROLAMINE 0.015 1/100 1

Drug Facts

Active Ingredient Purpose

Ethyl Alcohol 62% Sanitizer

Uses:

To decrease bacteria on the skin that could cause diseases

Recommended for repeated use

Warnings:

For external use only-hands. Use only as directed. Excessive use or prolonged exposure may cause irritation to skin. Discontinue use if rash, redness, or itching occurs.

Flammable. Keep away from heat and flame.

When using this product

- Keep out of eyes. In case of contacting with eyes, immediately flash with water and call a doctor.
- Avoid contacting with a broken skin.

STOP USE

Stop using and ask a doctor if irritation or redness develops.

Keep out of reach of children.

In case of accidental ingestion, seek professional assistance or contact a Poison Control Center immediately.

Directions

Adults and children two years and over:

- Apply to hands
- Allow skin to dry without wiping

Other Information

- Do not store in temperatures over 118F
- Children under six years of age should be supervise while using this product.
- May discolor certain fabrics.

Inactive Ingredients

water, glycerin, carbomer, triethanolamine, aloe barbadensis extract, and vitamin E

PACKAGE LABEL

labe

PACKAGE LABEL

outer